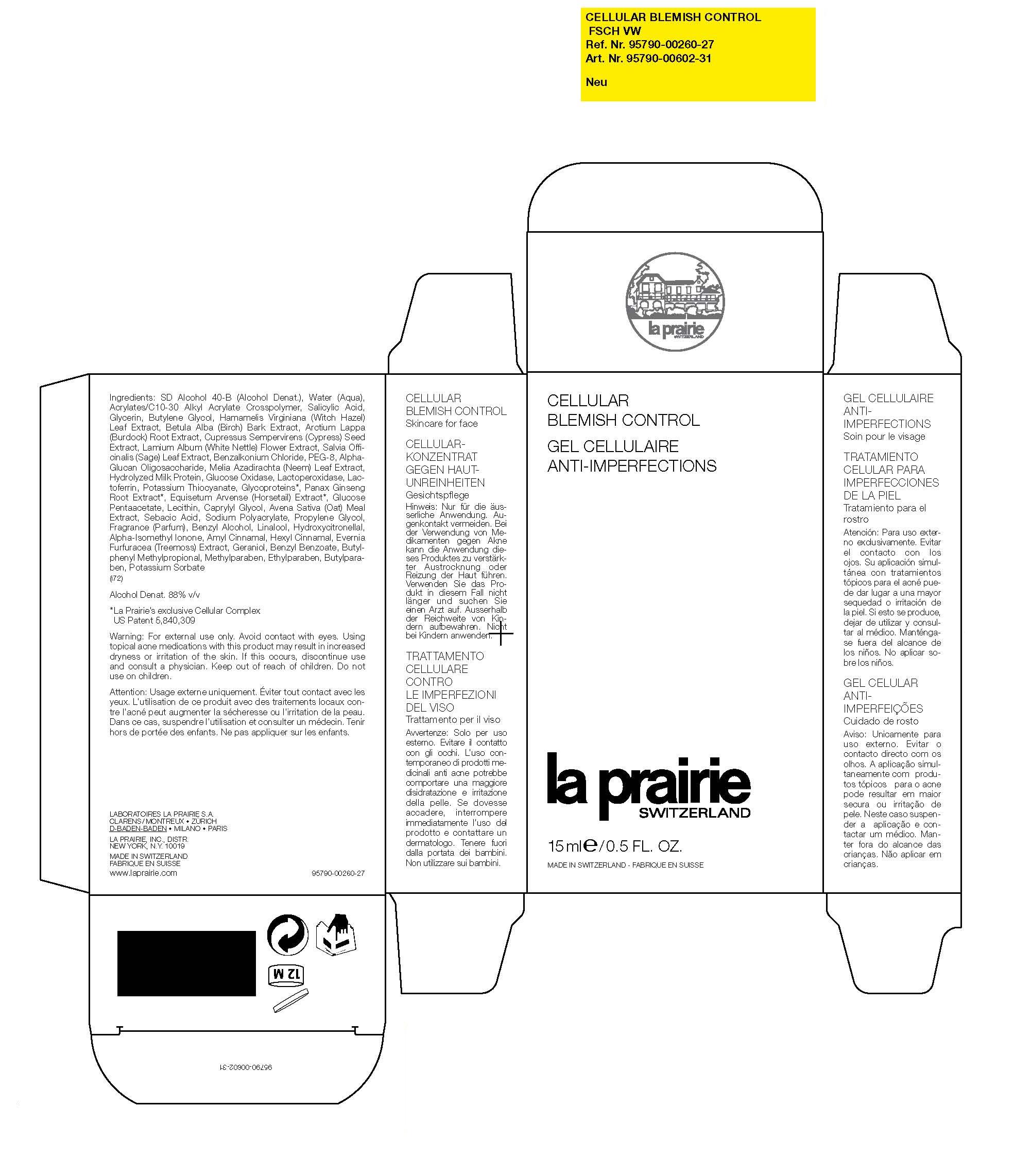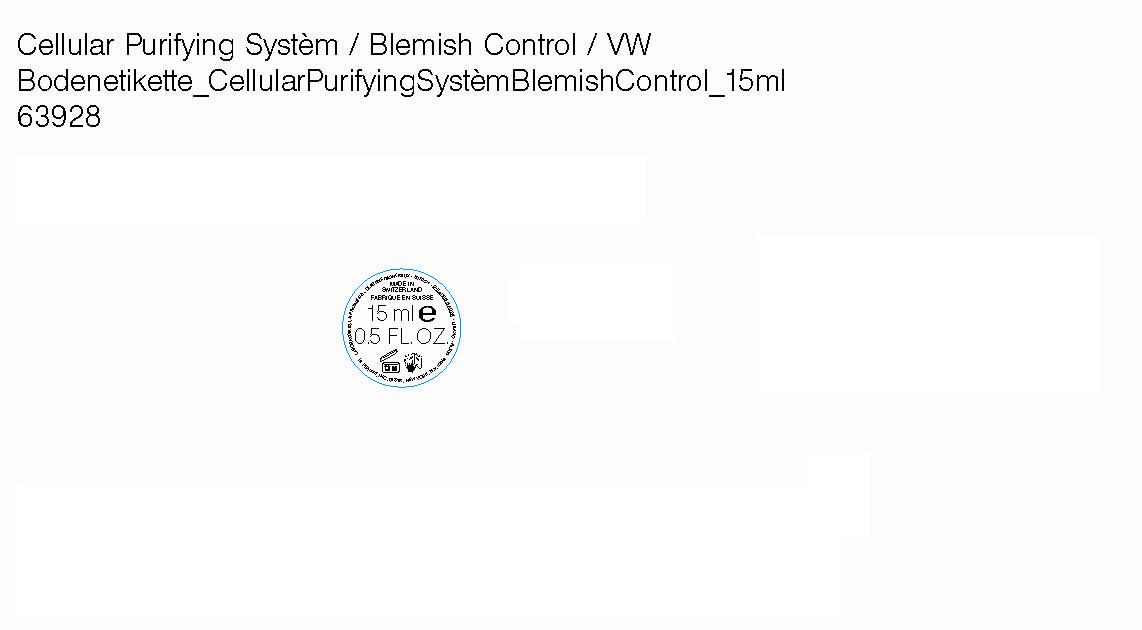 DRUG LABEL: La Prairie Switzerland 
NDC: 59614-311 | Form: CREAM
Manufacturer: Juvena Produits de Beaute GMBH
Category: otc | Type: HUMAN OTC DRUG LABEL
Date: 20100602

ACTIVE INGREDIENTS: SALICYLIC ACID 2.0 mCi/100 mL

Cellular Blemish Control

Active Ingredients:

Salicylic Acid 2.0%

WARNINGS

Warnings: For external use only. Avoid contact with eyes. Using topical acne medications with this product may result in increased dryness or irritation of the skin. If this occurs, discontinue use and consult a physician. Keep out of reach of children. Do not use on children.

INACTIVE INGREDIENT

Inactive Ingredients: SD Alcohol 40-B (Alcohol Denat.), Water (Aqua), Acrylates/C10-30 Alkyl Acrylate Crosspolymer, Salicylic Acid, Glycerin, Butylene Glycol, Hamamelis Virginiana (Witch Hazel) Leaf Extract, Betula Alba (Birch) Bark Extract, Arctium Lappa (Burdock) Root Extract, Cupressus Sempervirens (Cypress) Seed Extract, Lamium Album (White Nettle) Flower Extract, Salvia Officinalis (Sage) Leaf Extract, Benzalkonium Chloride, PEG-8, Alpha-Glucan Oligosaccharide, Melia Azadirachta (Neem) Leaf Extract, Hydrolyzed Milk Protein, Glucose Oxidase, Lactoperoxidase, Lactoferrin, Potassium Thiocyanate, Glycoproteins, Panax Ginseng Root Extract, Equisetum Arvense (Horsetail) Extract, Glucose Pentaacetate, Lecithin, Caprylyl Glycol, Arvena Sativa (Oat) Meal Extract, Sebacic Acid, Sodium Polyacrylate, Propylene Glycol, Fragrance (Parfum), Benzyl Alcohol, Linalool, Hydroxycitronellal, Alpha-Isomethyl Ionone, Amyl Cinnamal, Hexyl Cinnamal, Evernia Furfuracea (Treemoss) Extract, Geraniol, Benzyl Benzoate, Butylphenyl Methylpropional, Methylparaben, Ethylparaben, Butylparaben, Potassium Sorbate

PACKAGE LABEL

La Prairie Switzerland

Cellular Blemish Control

15 ml / 0.5 FL.OZ.